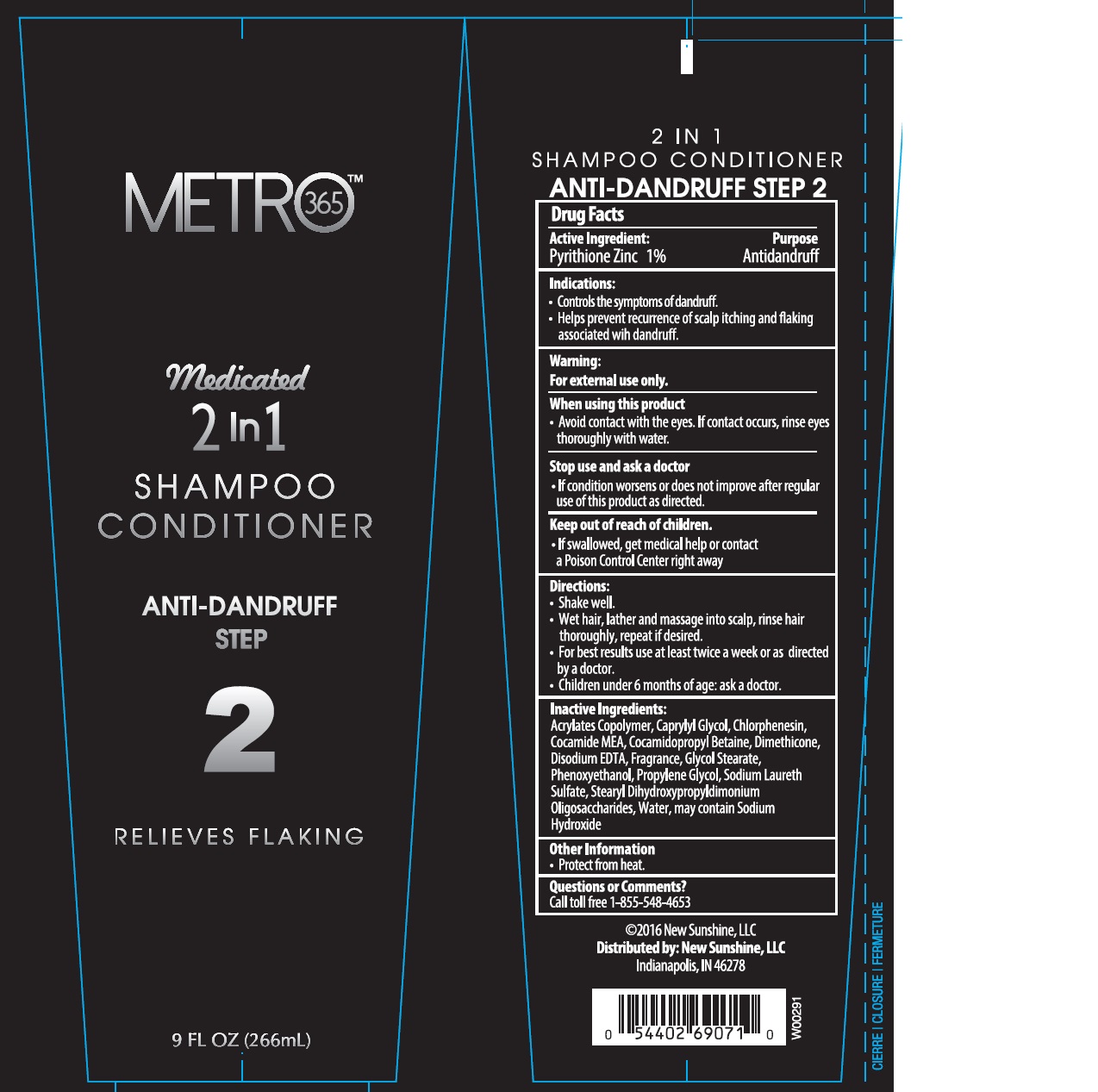 DRUG LABEL: Australian Gold
NDC: 58443-0242 | Form: SHAMPOO
Manufacturer: Prime Enterprises Inc.
Category: otc | Type: HUMAN OTC DRUG LABEL
Date: 20200117

ACTIVE INGREDIENTS: PYRITHIONE ZINC 10.32 mg/1 mL
INACTIVE INGREDIENTS: CHLORPHENESIN; COCAMIDOPROPYL BETAINE; DIMETHICONE; EDETATE DISODIUM; GLYCOL STEARATE; PHENOXYETHANOL; SODIUM HYDROXIDE; SODIUM LAURETH SULFATE; CARBOMER INTERPOLYMER TYPE A (ALLYL SUCROSE CROSSLINKED); CAPRYLYL GLYCOL; WATER; GUAR HYDROXYPROPYLTRIMONIUM CHLORIDE (1.7 SUBSTITUENTS PER SACCHARIDE); COCO MONOETHANOLAMIDE

Australian Gold Metro 365 Medicated 2 in 1 Anti - Dandruff

Active Ingredients

Pyrithione Zinc 1%

Purpose

Antidandruff

Indications

- Controls the symptoms of dandruff.
- Helps prevent recurrence of scalp itching and flaking associated with antidandruff.

Warnings

For external use only.

When using this product

- Avoid contact with the eyes. If contact occurs, rinse eyes thouroughly with water.

Stop use and ask a doctor

- If condition worsens or does not improve after regular use of this product as directed.

Keep out of reach of children.

If swallowed, get medical help or contact a Poison Control Center right away.

Directions

- Shake well
- Wet hair, lather and massage into scalp, rinse hair thoroughly, repeat if desired.
- For best results use at least twice a week or as directed by a doctor.
- Children under 6 months of age: ask a doctor.

INACTIVE INGREDIENT

Acrylates Copolymer, Caprylyl Glycol, Chlorphenesin, Cocamide MEA, Cocamidopropyl Betaine, Dimethicone, Disodium EDTA, Fragrance, Glycol Stearate, Phenoxyethanol, Propylene Glycol, Sodium Hydroxide, Sodium Laureth Sulfate, Stearyl Dihydroxypropyldimonium Oligosaccharides, Water

Other Information

- Protect from heat.

Questions or Comments?

Call toll free 1-855-548-4653